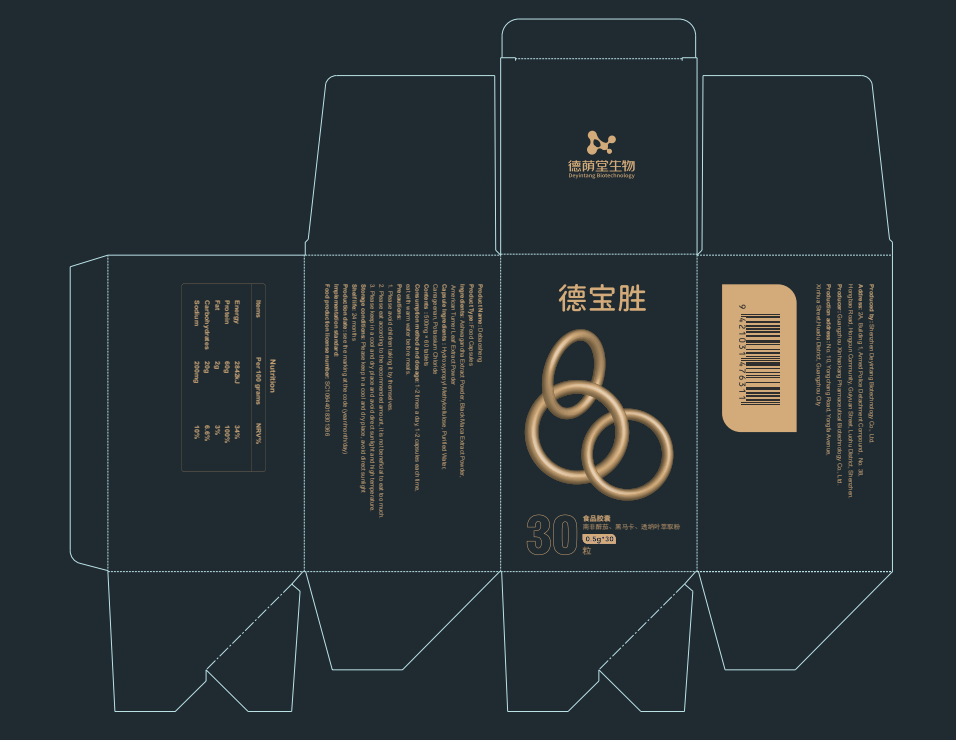 DRUG LABEL: Debaosheng
NDC: 82570-012 | Form: CAPSULE
Manufacturer: Shenzhen Deyintang Biotechnology Co., Ltd.
Category: otc | Type: HUMAN OTC DRUG LABEL
Date: 20220221

ACTIVE INGREDIENTS: LEPIDIUM MEYENII WHOLE 10 g/100 g; WITHANIA SOMNIFERA ROOT 52 g/100 g; TURNERA DIFFUSA LEAF 10 g/100 g
INACTIVE INGREDIENTS: CARRAGEENAN; POTASSIUM CHLORIDE; HYPROMELLOSES

ACTIVE INGREDIENT

Ashwagandha Extract Powder, Black Maca Extract Powder,American Turner Leaf Extract Powder

INACTIVE INGREDIENT

Hydroxypropyl Methylcellulose, Purified Water,Carrageenan, Potassium Chloride

PURPOSE

health care

Please avoid children taking it by themselves.

Consumption method and dosage

1-2 times a day, 1-2 capsules each time,eat with warm water before meals.

INDICATIONS AND USAGE

Please eat according to the recommended amount,it is not beneficial to eat too much.

Storage conditions

Please keep in a cool and dry place, avoid direct sunlight

WARNINGS

1.Please avoid children taking it by themselves.
2.Please eat according to the recommended amount,it is not beneficial to eat too much.
3.Please keep in a cool and dry place and avoid directsunlight and high temperature.